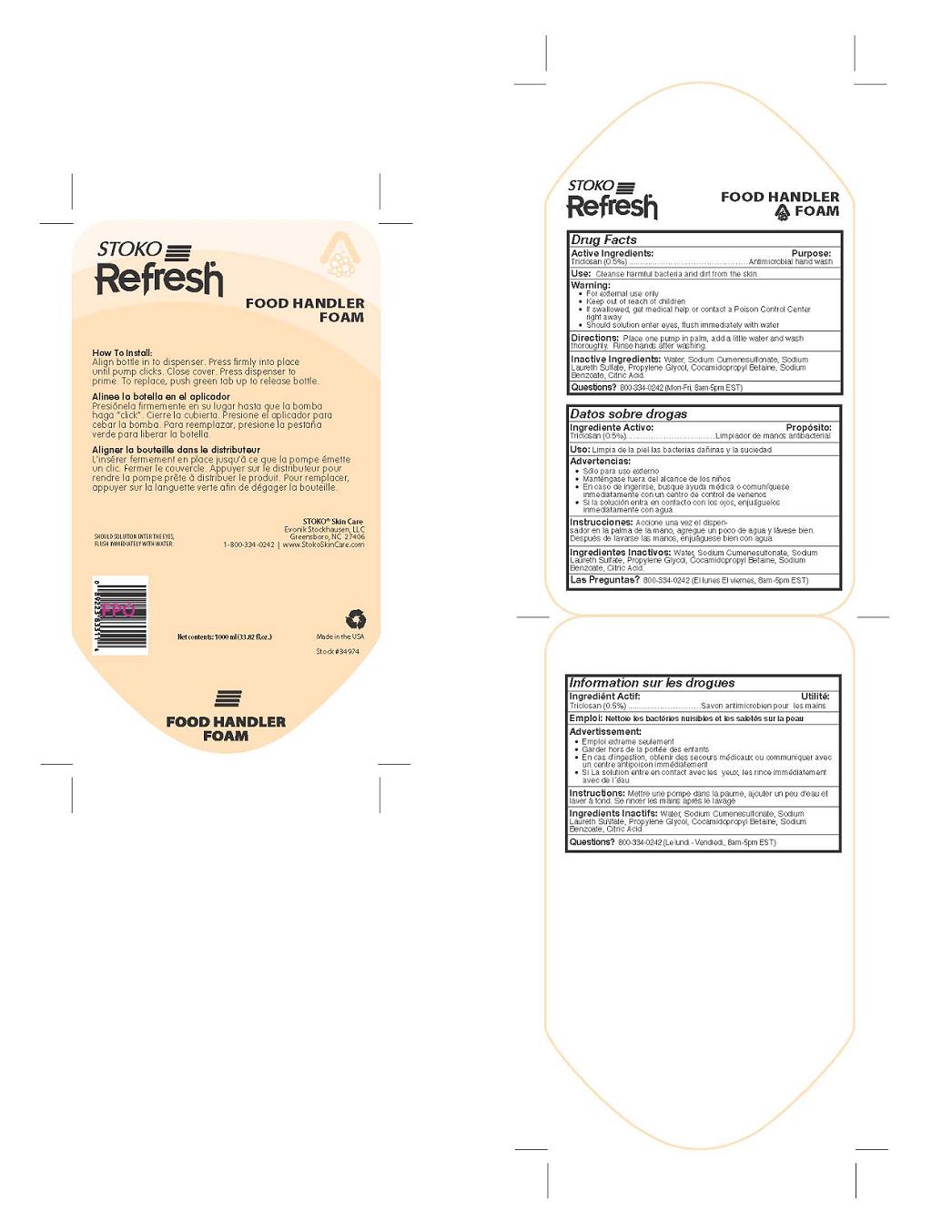 DRUG LABEL: Stoko Refresh Food Handler Foam
NDC: 64064-105 | Form: LIQUID
Manufacturer: Evonik Stockhausen, LLC
Category: otc | Type: HUMAN OTC DRUG LABEL
Date: 20110221

ACTIVE INGREDIENTS: Triclosan 0.5 g/100 mL
INACTIVE INGREDIENTS: Water; Sodium Cumenesulfonate; Sodium Laureth Sulfate; Propylene Glycol; Cocamidopropyl Betaine; Sodium Benzoate; Citric Acid Monohydrate

Drug Facts

Active Ingredients

Triclosan (0.5%)

Purpose

Antimicrobial hand wash

Use

Cleanse harmful bacteria and dirt from the skin.

Warning

- For external use only
- If swallowed, get medical help or contact a Poison Control Center right away
- Should solution enter eyes, flush immediately with water

- Keep out of reach of children

Directions

Place one pump in palm, add a little water and wash thoroughly. Rinse hands after washing.

Inactive Ingredients

Water, Sodium Cumenesulfonate, Sodium Laureth Sulfate, Propylene Glycol, Cocamidopropyle Betaine, Sodium Benzoate, Citric Acid.

Questions?

800-334-0242 (Mon-Fri, 8am-5pm EST)

Principal Display Panel

Stoko

Refresh

Food Handler

Foam

How To Install:

Align bottle in to dispenser. Press firmly into place

until pump clicks. Close cover. Press dispenser to

prime. To replace, push green tab up to release bottle.

Aligner la bouteille dans le distributeur

L'inserer fermement en place jusqu'a ce que la pompe emette

un clic. Fermer le couvercle. Appuyer sur le distributeur pour

rendre la pompe prete a distribuer le produit. Pour remplacer,

appuyer sur la languette verte afin de degager la bouteille.

Alinee la botella en el aplicador

Presionela firmemente en su lugar hasta que la bomba

haga "click". Cierre la cubierta. Presione el aplicador para

cebar la bomba. Para reemplazar, presione la pestana

verde para liberar la botella.

Should Solution Enter The Eyes,

Flush Immediately With Water.

Stoko Skin Care

Evonik Stockhausen, LLC

Greensboro, NC 27406

1-800-334-0242 I www.StokoSkinCare.com

Made in the USA

Stock#34974

Net contents: 1000 ml (33.82 fl. oz.)